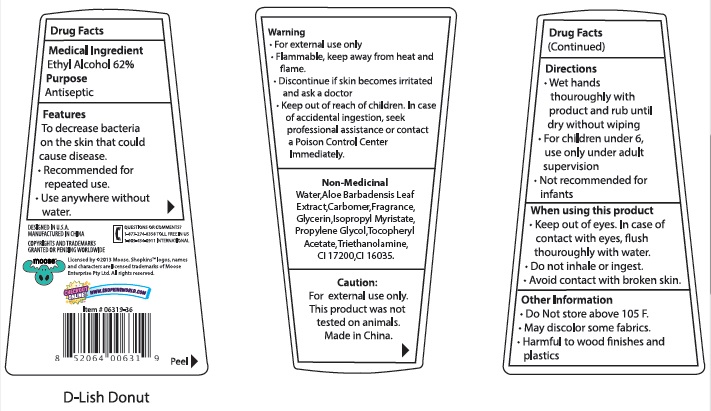 DRUG LABEL: Shopkins 3D Hand Sanitizer DLish Donut
NDC: 70108-002 | Form: GEL
Manufacturer: Ashtel Studios, Inc.
Category: otc | Type: HUMAN OTC DRUG LABEL
Date: 20191231

ACTIVE INGREDIENTS: ALCOHOL 62 g/100 g
INACTIVE INGREDIENTS: WATER; ISOPROPYL ALCOHOL; GLYCERIN; CARBOMER COPOLYMER TYPE A (ALLYL PENTAERYTHRITOL CROSSLINKED); AMINOMETHYLPROPANOL; PROPYLENE GLYCOL; ISOPROPYL MYRISTATE; ALOE VERA LEAF; .ALPHA.-TOCOPHEROL ACETATE

Shopkins 3D Hand Sanitizer DLish Donut

Mecicical Ingredient

Ethyl Alcohol 62%

Purpose

Antiseptic

PURPOSE

Features

To decrease bacteria on the skin that could cause disease.

- Recommended for repeated use.
- Use anywhere without water.

Keep out of reach of children. In case of accidental ingestion, seek professional assistance or contact a Poison Control Center immediately.

DIRECTIONS

Wet hands thoroughly wih product and rub until dry without wiping.

For children under 6 use only under adult supervision.

Not recommended for infants

Directions

- Wet hands thoroughly with product and rub until dry without wiping
- For children under 6, use only under adult supervision.
- Not recommended for infants

Warning

- For external use only - hands
- Flammable, keep away from heat and flame
- Discontinue if skin becomes irritated and ask a doctor

CAUTION: For external use only. This product was not tested on animals.

When using this product

- Keep out of eyes. In case of contact with eyes, flush thoroughly with water.
- Do not inhale or ingest.
- Avoid contact with broken skin.

Other information

- Do not store above 105°F.
- May discolor some fabrics.
- Harmful to wood finishes and plastics.

INACTIVE INGREDIENT

Non-Medicinal

water, isopropyl alcohol, glycerin, carbomer, aminomethyl propanol, parfum, propylene glycol, isopropyl myristate, aloe barbadensis leaf juice, tacopheryl acetate